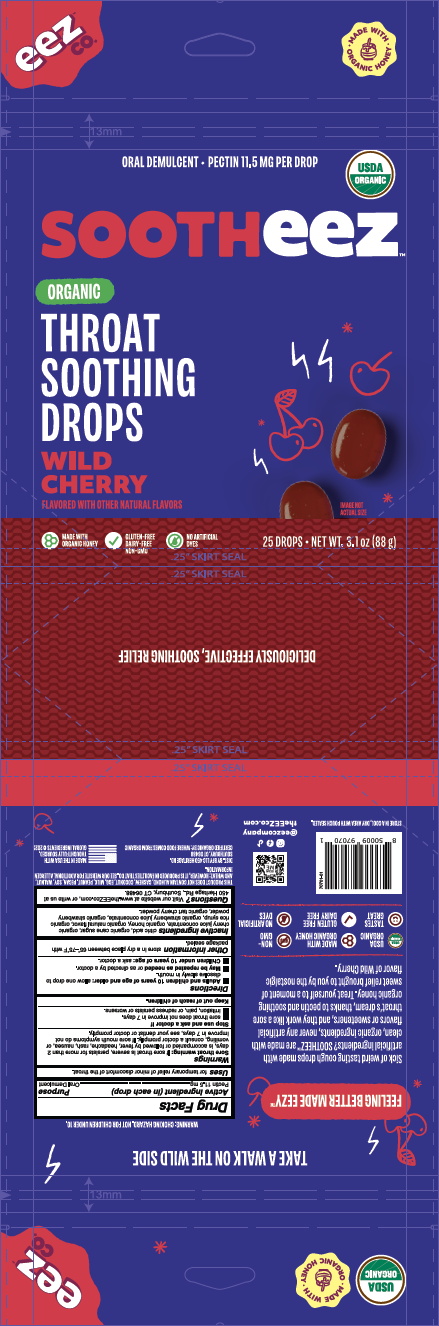 DRUG LABEL: Sootheez Organic Wild Cherry
NDC: 72427-3714 | Form: LOZENGE
Manufacturer: BFY LLC
Category: otc | Type: HUMAN OTC DRUG LABEL
Date: 20260106

ACTIVE INGREDIENTS: PECTIN 11.5 mg/3.5 g
INACTIVE INGREDIENTS: HONEY

Sootheez Organic Wild Cherry

Sootheez Wild Cherry - Organic 25CT 3714-2

Drug Facts

Active Ingredient (in each drop)

Pectin 11.5 mg

Purpose

Oral Demulcent

Uses

for temporary relief of minor discomfort of the throat.

Warnings

Sore throat warning: if sore throat is severe, persists for more than 2 days, is accompanied or followed by fever, headache, rash, nausea, or vomitting, consult a doctor promptly. If sore mouth symptoms do not improve in 7 days, see your dentist or doctor promptly.

Stop use and ask a doctor if

- sore throat does not improve in 7 days.
- irritation, pain, or redness persists or worsens.

Keep out of reach of children.

Keep out of reach of children.

Directions

- Adults and children 10 years of age and older: allow one drop to dissolve slowly in mouth.
- May be repeated as needed or as directed by a doctor.
- Children under 10 years of age: ask a doctor.

Other information

store in a dry place between 65°-75°F with pouch sealed.

Inactive ingredients

citric acid, organic cane sugar, organic cherry juice concentrate, organic honey, organic natural flavor, organic rice syrup, organic strawberry juice concentrate, organic strawberry powder, organic tart cherry powder.

Questions?

Visit our website at www.theEEZco.com, or write us at 450 Heritage Rd., Southbury, CT 06488.